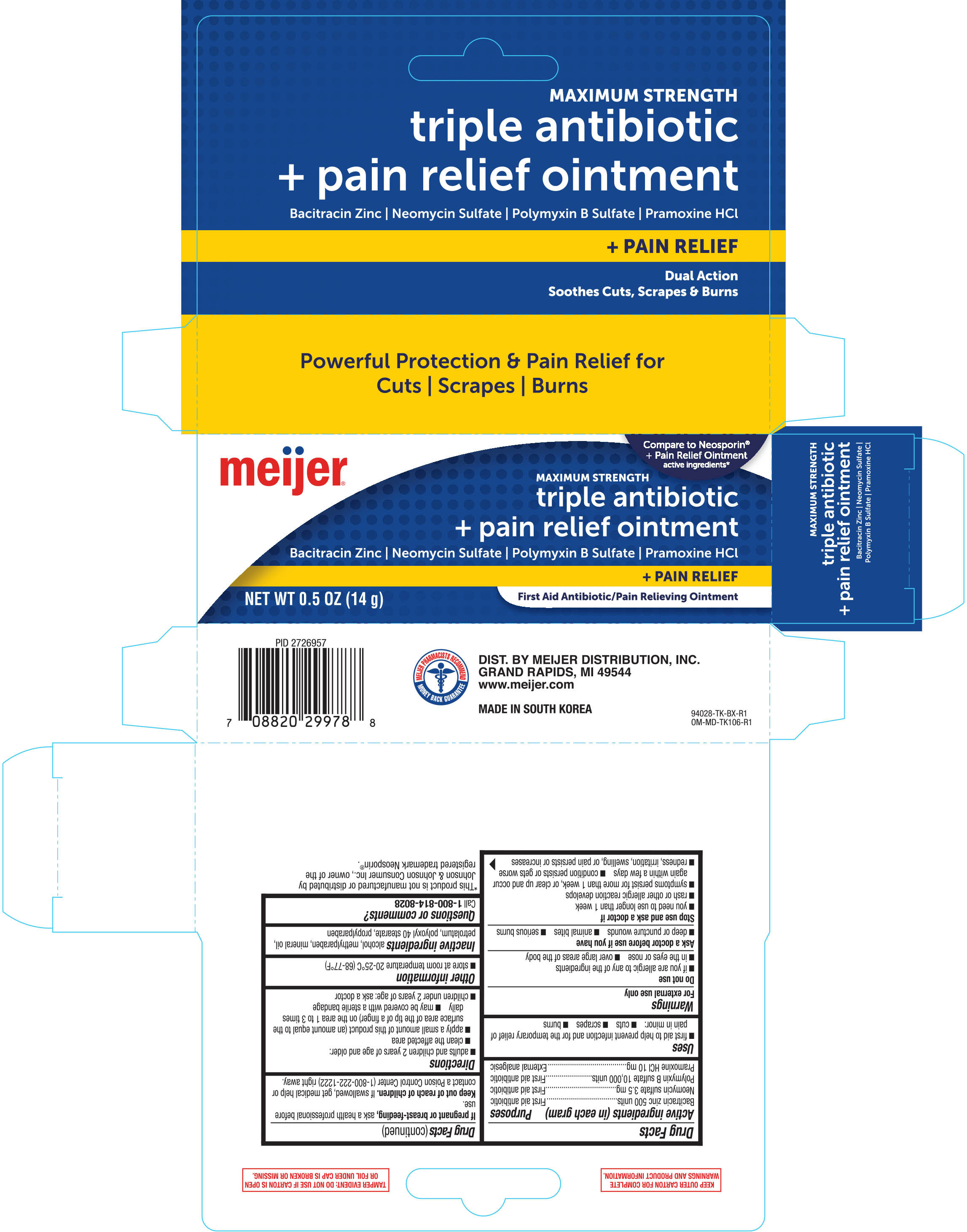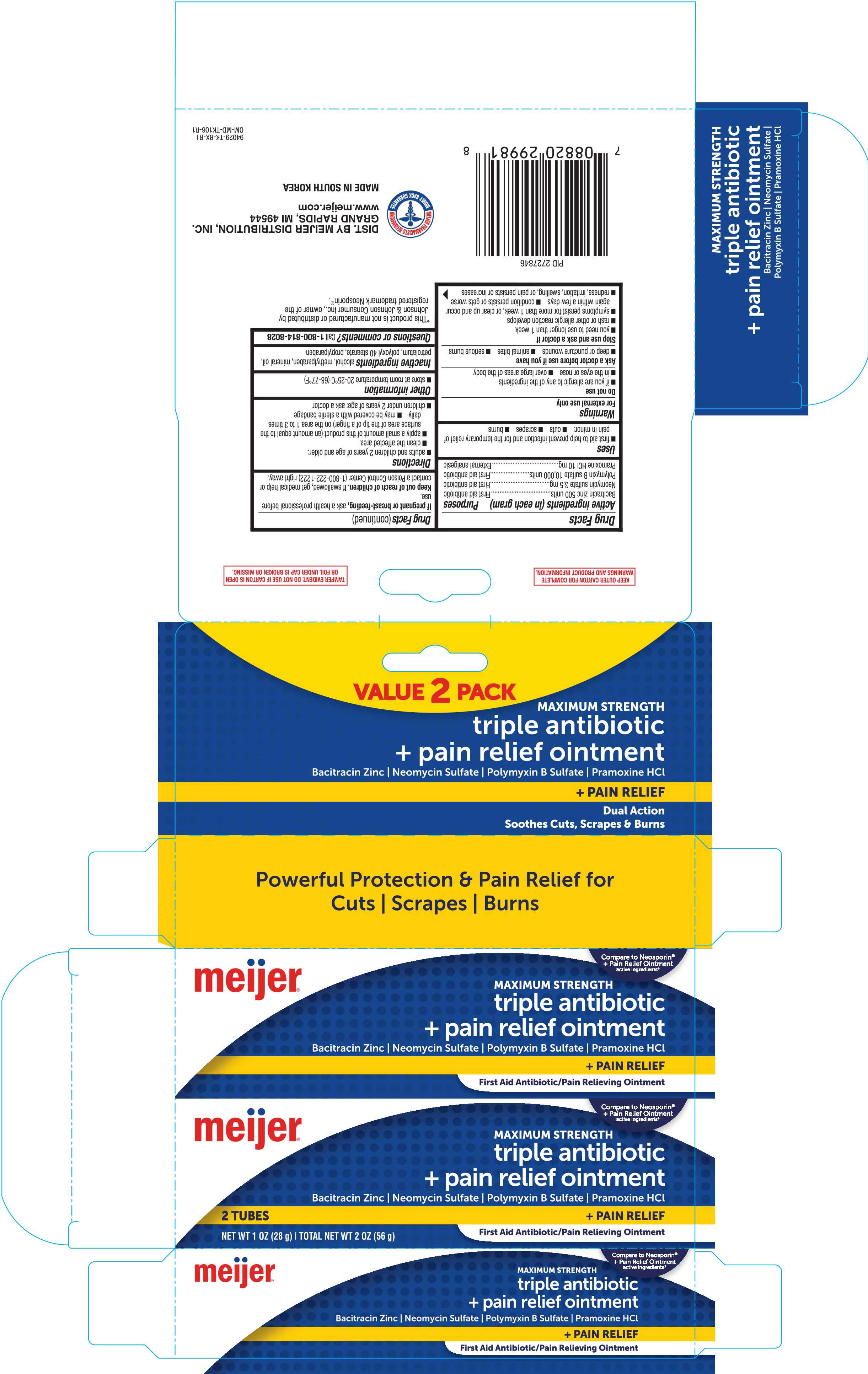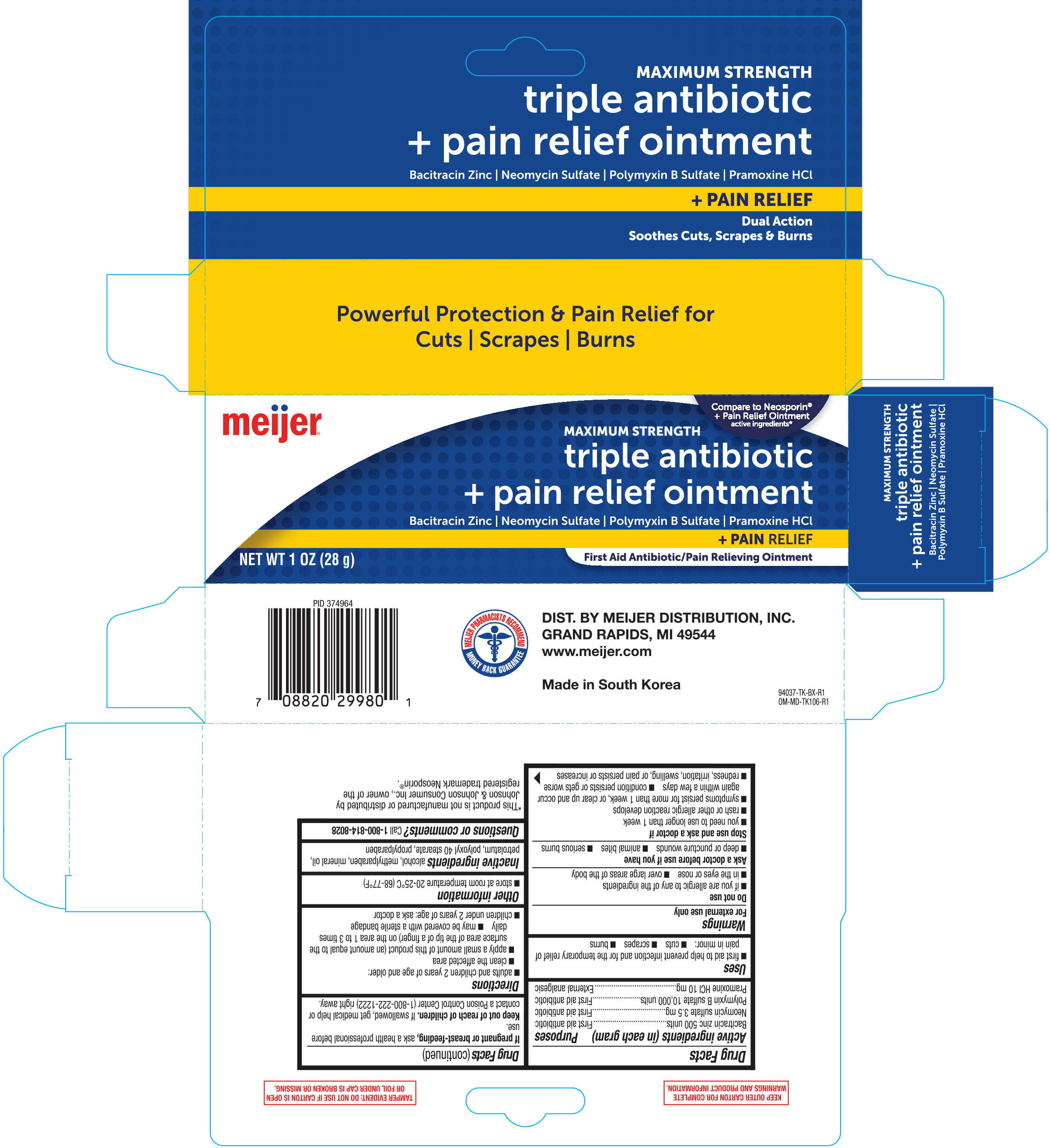 DRUG LABEL: triple antibiotic plus
NDC: 41250-961 | Form: OINTMENT
Manufacturer: Meijer, Inc.
Category: otc | Type: HUMAN OTC DRUG LABEL
Date: 20181218

ACTIVE INGREDIENTS: NEOMYCIN SULFATE 3.5 mg/1 g; PRAMOXINE HYDROCHLORIDE 10 mg/1 g; BACITRACIN ZINC 500 [iU]/1 g; POLYMYXIN B SULFATE 10000 [iU]/1 g
INACTIVE INGREDIENTS: MINERAL OIL; ALCOHOL; METHYLPARABEN; PROPYLPARABEN; POLYOXYL 40 STEARATE; PETROLATUM

Meijer Triple Antibiotic Plus Pain Relief Ointment 0.5oz (94028, 2018)
Meijer Triple Antibiotic Plus Pain Relief Ointment 1.0oz (94037, 2018)
Meijer Triple Antibiotic Plus Pain Relief Ointment 1.0oz Twin (94029, 2018)

Active ingredients (in each gram) Purposes

Bacitracin zinc 500 units........................First Aid antibiotic

Neomycin sulfate 3.5 mg.......................First Aid antibiotic

Polymyxin B sulfate 10,000 units...........First Aid antibiotic

Pramoxine HCl 10 mg............................First Aid antibiotic

Uses

- first aid to help prevent infection and for the temporary relief of pain in minor:
- cuts
- scrapes
- burns

Warnings

For external use only

Do not use

- if you are allergic to any of the ingredients
- in the eyes or nose
- over large areas of the body

Ask a doctor before use if you have

- deep or puncture wounds
- animal bites
- serious burns

Stop use and ask a doctor if

- you need to use longer than 1 week
- rash or other allergic reaction develops
- symptoms persist for more than 1 week or clear up and occur again within a few days
- condition persists or gets worse
- redness, irritation, swelling, or pain persists or increases

PREGNANCY OR BREAST FEEDING

If pregnant or breast-feeding, ask a health professional before use.

Keep out of reach of children. If swallowed, get medical help or contact a Poison Control Center (1-800-222-1222) right away.

Directions

- adults and children 2 years of age and older:
- clean the affected area
- apply a small amount of this product (an amount equal to the surface area of the tip of a finger) on the area 1 to 3 times
- may be covered with a sterile bandage
- children under 2 years of age: ask a doctor

Other information

- store at room temperature 20-25°C (68-77°F)

INACTIVE INGREDIENT

Inactive ingrdients alcohol, methylparaben, mineral oil, petrolatum, polyoxl 40 stearate, propylparaben

Questions or comments?

Call 1-800-814-8028

DOSAGE AND ADMINISTRATION

DIST. BY MEIJER DISTRIBUTION, INC.

GRAND RAPIDS, MI 49544

www.meijer.com

MADE IN SOUTH KOREA